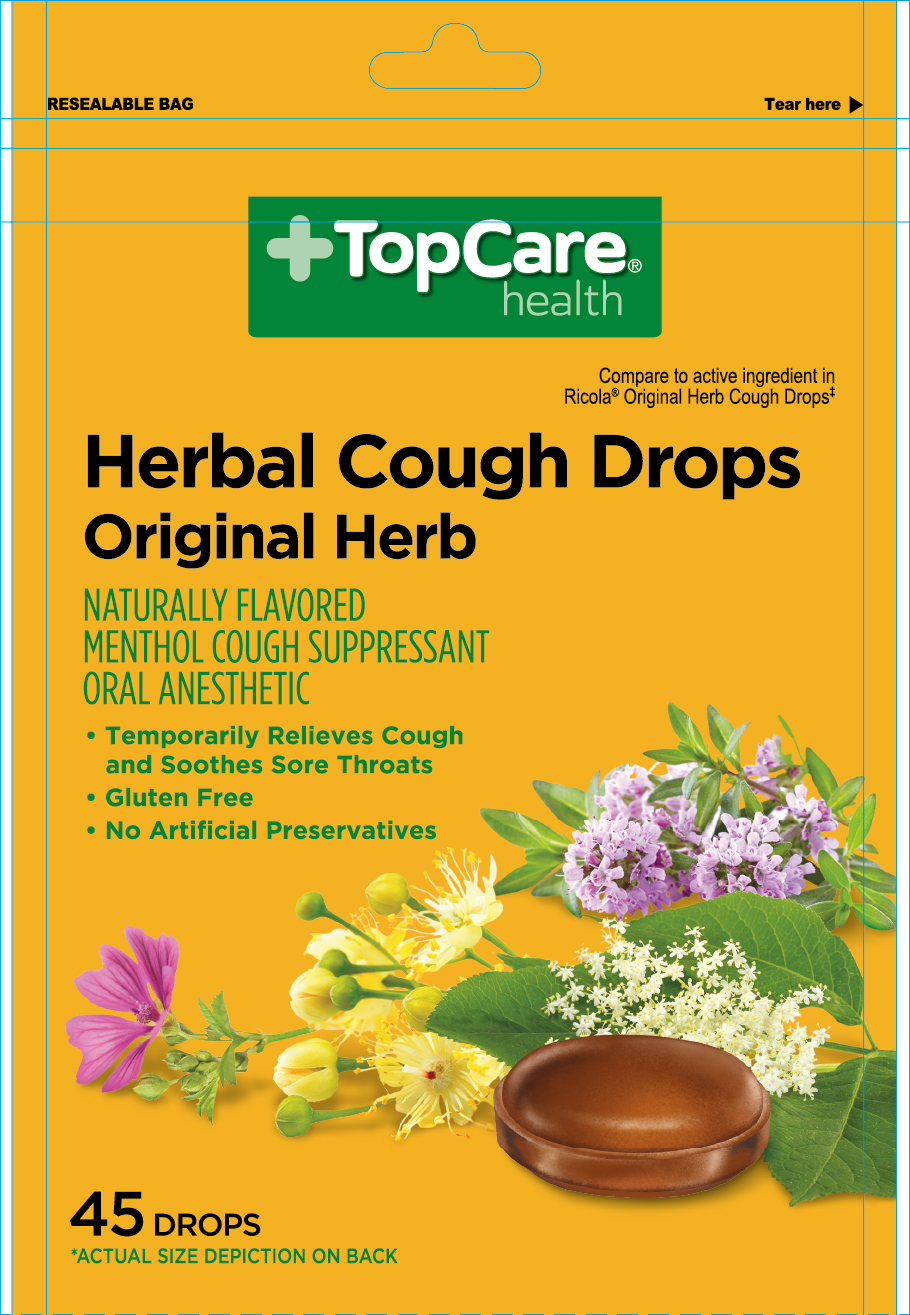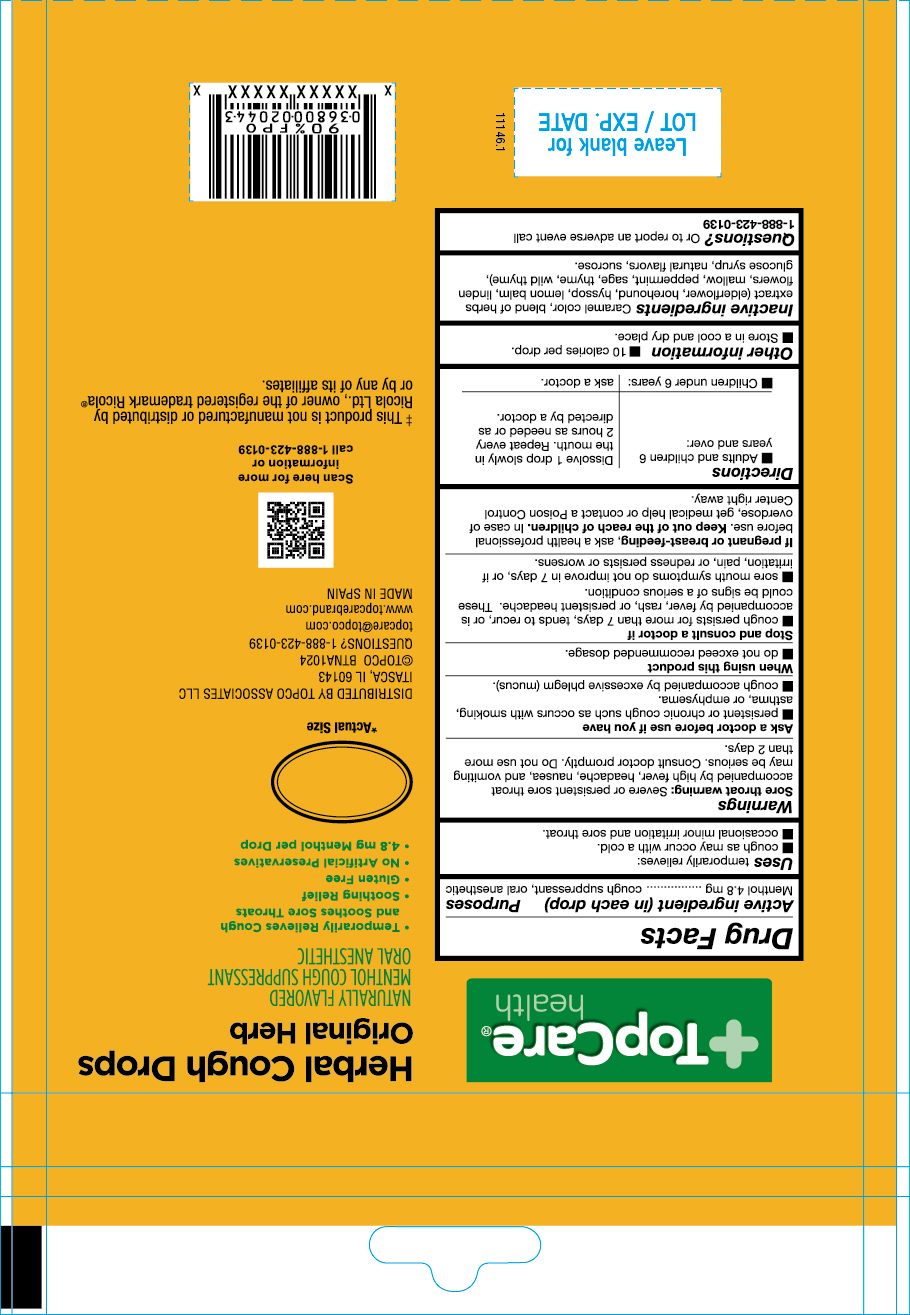 DRUG LABEL: Herbal Cough Drops Original Herb
NDC: 76162-061 | Form: PASTILLE
Manufacturer: Topco Associates LLC
Category: otc | Type: HUMAN OTC DRUG LABEL
Date: 20250306

ACTIVE INGREDIENTS: MENTHOL 4.8 mg/1 1
INACTIVE INGREDIENTS: SAMBUCUS NIGRA FLOWER; LEMON BALM OIL; THYME; CARAMEL; FLAVONE; SUCROSE; GLUCOSE; TILIA CORDATA FLOWER; MALVA NEGLECTA WHOLE; WILD THYME; PEPPERMINT; SAGE; HYSSOPUS OFFICINALIS WHOLE; HOREHOUND

USES

- cough as may occur with a cold
- ocassional minor irritation and sore throat

Menthol

Active Ingredient

Menthol 4.8 mg

Stop and Consult a Doctor if

- cough persists for more than 7 days, tends to recur, or is accompanied by fever, rash or persistent headache. These could be signs of a serious condition.
- Sore mouth symptons do not improve in 7 days, or if irritation, pain, or redness persists or worsens.

If pregnant or breast feeding, ask a health professional before use.

Keep out of the reach of children

Keep out of the reach of chilcren. In case of overdose, get medical help or contact a Poison Control Center right away.

Questions?

Questions? or to report an adverse event call 1-888-423-0139

When using this product

- do not exceed recomended dosage

Other information

- 10 calories per drop
- Store in a cool and dry place

Warnings

Sore throat warning: Severe or persisten sore throat accompanied by high fever, headache, nausea, and vomiting may be serious. Consult a doctor promptly. Do not use more than 2 days.

Inactive Ingredients

Elderflower, Horehound, Hyssop, Lemon balm, Linden flowers, Mallow, Peppermint, Sage, Thyme, Wild thyme, Glucose syrup, Sucrose, Caramel color, Natural flavors

Directions

- Adults and children 6 years and over: dissolve 1 drop slowly in the mouth. Repeat every 2 hours as needed or as directed by the doctor
- Children under 6 years: as a doctor

Indications & Usage Section

Uses temporarily relieves:

- cough as may occur with a cold
- ocassional minor irritation and sore throat